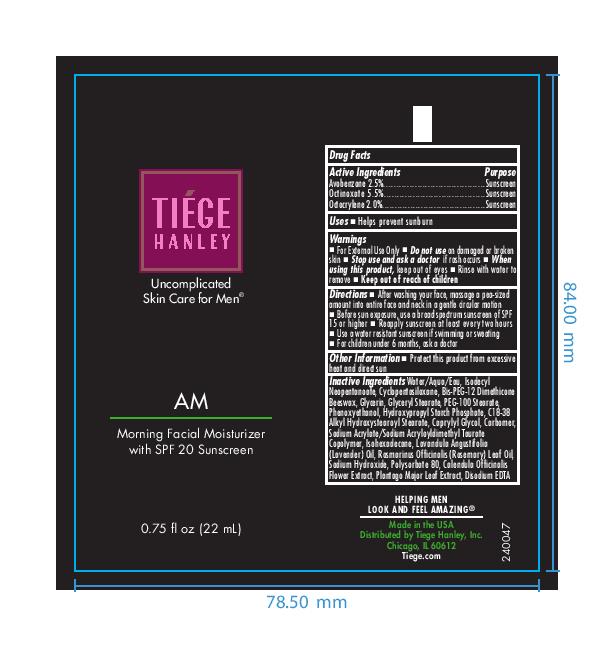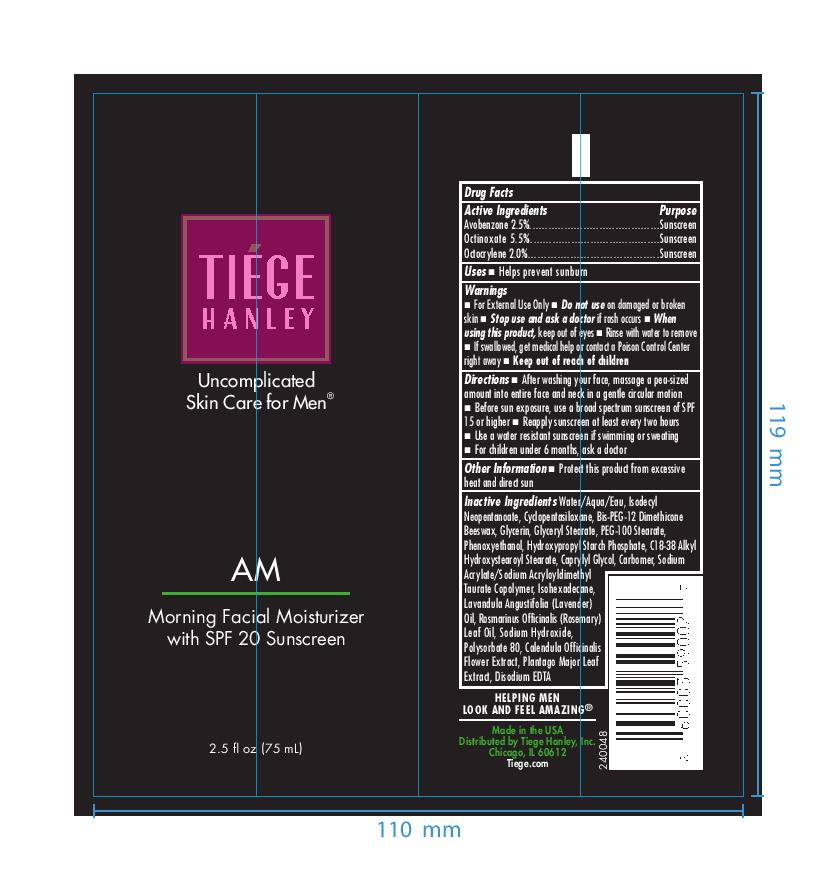 DRUG LABEL: Tiege Hanley AM Morning Facial Moisturizer with SPF 20
NDC: 71714-001 | Form: LOTION
Manufacturer: TIEGE HANLEY, Inc
Category: otc | Type: HUMAN OTC DRUG LABEL
Date: 20250724

ACTIVE INGREDIENTS: AVOBENZONE 25 mg/1 mL; OCTINOXATE 55 mg/1 mL; OCTOCRYLENE 20 mg/1 mL
INACTIVE INGREDIENTS: WATER; CALENDULA OFFICINALIS FLOWER; BIS-PEG-12 DIMETHICONE (70 MPA.S); GLYCERIN; SODIUM ACRYLATE/SODIUM ACRYLOYLDIMETHYLTAURATE COPOLYMER (4000000 MW); PLANTAGO MAJOR LEAF; LAVENDER OIL; ISODECYL NEOPENTANOATE; HYDROXYPROPYL CORN STARCH (5% SUBSTITUTION BY WEIGHT); CARBOMER 940; GLYCERYL MONOSTEARATE; PEG-100 STEARATE; PHENOXYETHANOL; CAPRYLYL GLYCOL; SODIUM HYDROXIDE; POLYSORBATE 80; EDETATE DISODIUM ANHYDROUS; TETRADECYLOCTADECYL STEARATE; CYCLOMETHICONE 5; ISOHEXADECANE; ROSEMARY OIL

Tiege Hanley AM Morning Facial Moisturizer with SPF 20
0.75 FL OZ (22ml) & 2.5 FL OZ (75 ml)

Active Ingredients
Avobenzene 2.5%
Octinoxate 5.5%
Octocrylene 2.0%

PURPOSE

SUNSCREEN

KEEP OUT OF REACH OF CHILDREN

■ If swallowed, get medical help or contact a Poison Control Center right away
■ Keep out of reach of children

Warnings
■ For External Use Only
■ Do not use on damaged or broken skin
■ Stop use and ask a doctor if rash occurs
■ When using this product, keep out of eyes
■ Rinse with water to remove
■ If swallowed, get medical help or contact a Poison Control Center right away
■ Keep out of reach of children

Directions
■ After washing your face, massage a pea-sized
amount into entire face and neck in a gentle circular motion
■ Before sun exposure, use a broad-spectrum sunscreen of SPF
15 or higher
■ Reapply sunscreen at least every two hours
■ Use a water-resistant sunscreen if swimming or sweating
■ For children under 6 months, ask a doctor

INDICATIONS AND USAGE

Uses ■ Helps prevent sunburn

INACTIVE INGREDIENT

Water

Isodecyl Neopentanoate

Cyclopentasiloxane

Bis-PEG-12 Dimethicone Beeswax

Glycerin

Glyceryl Stearate

PEG-100 Stearate

Phenoxyethanol

Hydroxypropyl Starch Phosphate

C18-38 Alkyl Hydroxystearoyl Stearate

Caprylyl Glycol

Carbomer

Sodium Acrylate/Sodium Acryloyldimethyl Taurate Copolymer

Isohexadecane

Lavandula Angustifolia (Lavender) Oil

Rosmarinus Officinalis (Rosemary) Leaf Oil

Sodium Hydroxide

Polysorbate 80

Calendula Officinalis Flower Extract

Plantago Major Leaf Extract

Disodium EDTA